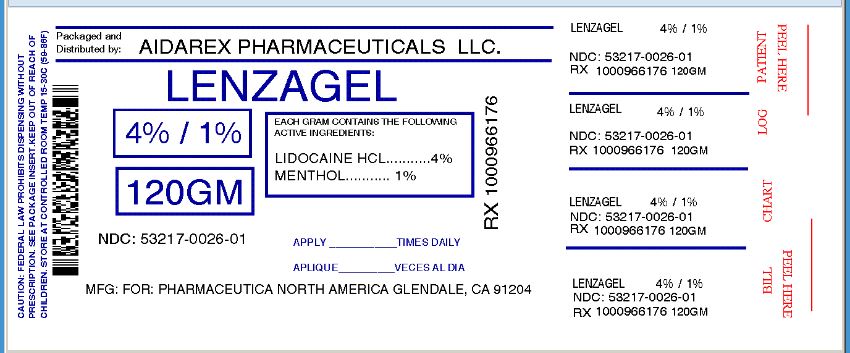 DRUG LABEL: LenzaGel
NDC: 53217-026 | Form: GEL
Manufacturer: Aidarex Pharmaceuticals LLC
Category: otc | Type: HUMAN OTC DRUG LABEL
Date: 20131002

ACTIVE INGREDIENTS: LIDOCAINE HYDROCHLORIDE 4 g/100 g; MENTHOL 1 g/100 g
INACTIVE INGREDIENTS: ALOE VERA LEAF; WATER; ARNICA MONTANA; INDIAN FRANKINCENSE; GREEN TEA LEAF; ETHYLHEXYLGLYCERIN; GLYCERIN; ISOPROPYL MYRISTATE; POLYETHYLENE GLYCOL 400; PHENOXYETHANOL; POLYSORBATE 80; SODIUM LAURYL SULFATE; TROLAMINE; FD&C BLUE NO. 1; FD&C YELLOW NO. 5

LenzaGel

Active Ingredients:

Lidocaine HCL 4.00%

Menthol 1.00%

Purpose

Topical Analgesic

External Analgesic

Uses:

For temporary relief of pain associated with minor cuts, scrapes and minor skin irritations.

Warnings

- For external use only
- Avoid contact with eyes
- Do not apply to open wounds or damaged skin.
- If symptoms persist for more than seven days, discontinue use and consult physician.

Keep out of reach of children.

If swallowed, consult physician.

- Do not bandage tightly
- If pregnant or breast feeding, contact physician prior to use.
- Do not use in large quantities, particularly over raw surfaces or blistered areas.

Directions

- Apply directly to effected area. Do not use more than four times per day.

Other Ingredients:

Aloe Barbadensis Leaf (Aloe Vera Juice) Gel, Aqua (Deionized Water), Arnica Montana Extract, Boswellia Serrata Extract, Camellia Sinensis Leaf (Green Tea) Extract, Carbomer, Ethylhexylglycerin, Glycerin, Isopropyl Myristate, PEG-8, Phenoxyethanol, Polysorbate-80, Sodium Lauryl Sulfate, Triethanolamine, FD C Blue 1, FD C Yellow 5.

PACKAGE LABEL PRINCIPAL DISPLAY PANEL

Repackaged By :
Aidarex Pharmaceuticals LLC,
Corona, CA 92880